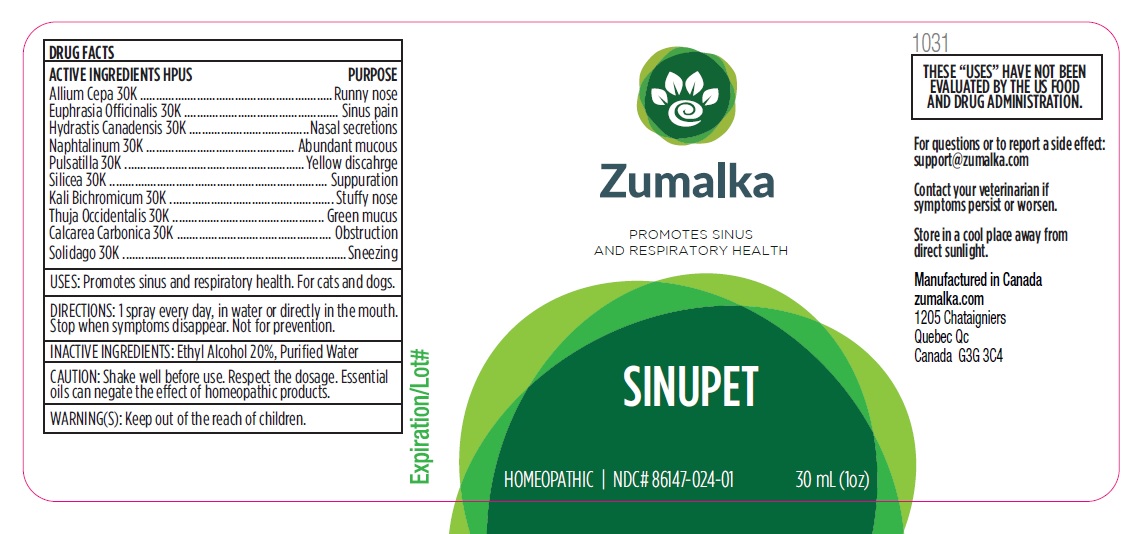 DRUG LABEL: SINUPET
NDC: 86147-024 | Form: LIQUID
Manufacturer: Groupe Cyrenne Inc.
Category: homeopathic | Type: OTC ANIMAL DRUG LABEL
Date: 20251120

ACTIVE INGREDIENTS: ONION 30 [kp_C]/30 mL; EUPHRASIA STRICTA 30 [kp_C]/30 mL; GOLDENSEAL 30 [kp_C]/30 mL; NAPHTHALENE 30 [kp_C]/30 mL; SILICON DIOXIDE 30 [kp_C]/30 mL; THUJA OCCIDENTALIS LEAFY TWIG 30 [kp_C]/30 mL; POTASSIUM DICHROMATE 30 [kp_C]/30 mL; PULSATILLA VULGARIS WHOLE 30 [kp_C]/30 mL; SOLIDAGO VIRGAUREA FLOWERING TOP 30 [kp_C]/30 mL; OYSTER SHELL CALCIUM CARBONATE, CRUDE 30 [kp_C]/30 mL
INACTIVE INGREDIENTS: WATER; ALCOHOL

Active ingredient Purpose

Allium Cepa 30k Runny nose

Euphrasia Officinalis 30k Sinus pain

Hydrastis Canadensis 30k Nasal secretions

Naphthalinum 30k Abundant mucous

Pulsatilla 30k Yellow discahrge

Silicea 30k Suppuration

Kali Bichromicum 30k Stuffy nose

Thuja Occidentalis 30k Green mucus

Calcarea Carbonica 30k Obstruction

Solidago 30k Sneezing

Uses

Promotes sinus and respiratory health. For cats and dogs only.

Warnings

Keep out of reach of children.

Direction

1 spray every day, in water or directly in the mouth. Stop when symptoms disappear. Not for prevention.

Inactive ingredient

Ethyl alcohol 20%, purified water

Cautions

Shake well before use. Respect the dosage. Essential oils can negate the effects of homeopathic products. Store in a cool place away from direct sunlight.